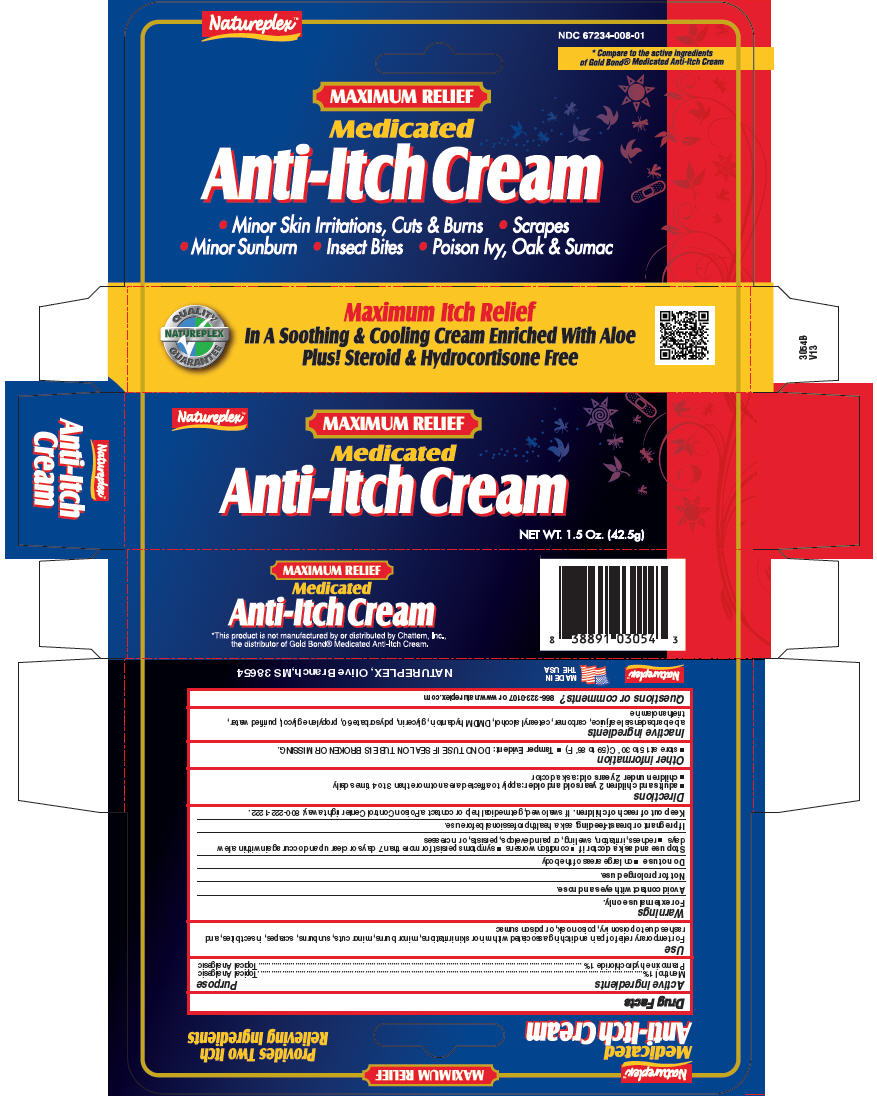 DRUG LABEL: Anti Itch 
NDC: 67234-008 | Form: CREAM
Manufacturer: Natureplex LLC
Category: otc | Type: HUMAN OTC DRUG LABEL
Date: 20250828

ACTIVE INGREDIENTS: Pramoxine Hydrochloride 10 mg/1 g; Menthol, Unspecified Form 10 mg/1 g
INACTIVE INGREDIENTS: ALOE VERA LEAF; CARBOMER HOMOPOLYMER TYPE C (ALLYL PENTAERYTHRITOL CROSSLINKED); DMDM HYDANTOIN; CETOSTEARYL ALCOHOL; POLYSORBATE 60; GLYCERIN; PROPYLENE GLYCOL; TROLAMINE; WATER

Anti-Itch Cream
Maximum Relief

Drug Facts

ACTIVE INGREDIENT

Active ingredients | Purpose
Menthol 1% | Topical Analgesic
Pramoxine hydrochloride 1% | Topical Analgesic

Use

For temporary relief of pain and itching associated with minor skin irritations, minor burns, minor cuts, sunburns, scrapes, insect bites, and rashes due to poison ivy, poison oak, or poison sumac

Warnings

For external use only.

Avoid contact with eyes and nose.

Not for prolonged use.

Do not use

- on large areas of the body

Stop use and ask a doctor if

- condition worsens
- symptoms persist for more than 7 days or clear up and occur again within a few days
- redness, irritation, swelling, or pain develops, persists, or increases

PREGNANCY OR BREAST FEEDING

If pregnant or breast-feeding, ask a health professional before use.

Keep out of reach of children. If swallowed, get medical help or contact a Poison Control Center right away: 800-222-1222.

Directions

- adults and children 2 years old and older: apply to affected area not more than 3 to 4 times daily
- children under 2 years old: ask a doctor

Other information

- store at 15 to 30° C (59 to 86° F)
- Tamper Evident: DO NOT USE IF SEAL ON TUBE IS BROKEN OR MISSING.

Inactive ingredients

aloe barbadensis leaf juice, carbomer, cetearyl alcohol, DMDM hydantoin, glycerin, polysorbate 60, propylene glycol, purified water, triethanolamine

Questions or comments?

866-323-0107 or www.natureplex.com

PRINCIPAL DISPLAY PANEL - 42.5 g Tube Box

Natureplex™

MAXIMUM RELIEF

Medicated
Anti-Itch Cream

NET WT. 1.5 Oz. (42.5g)